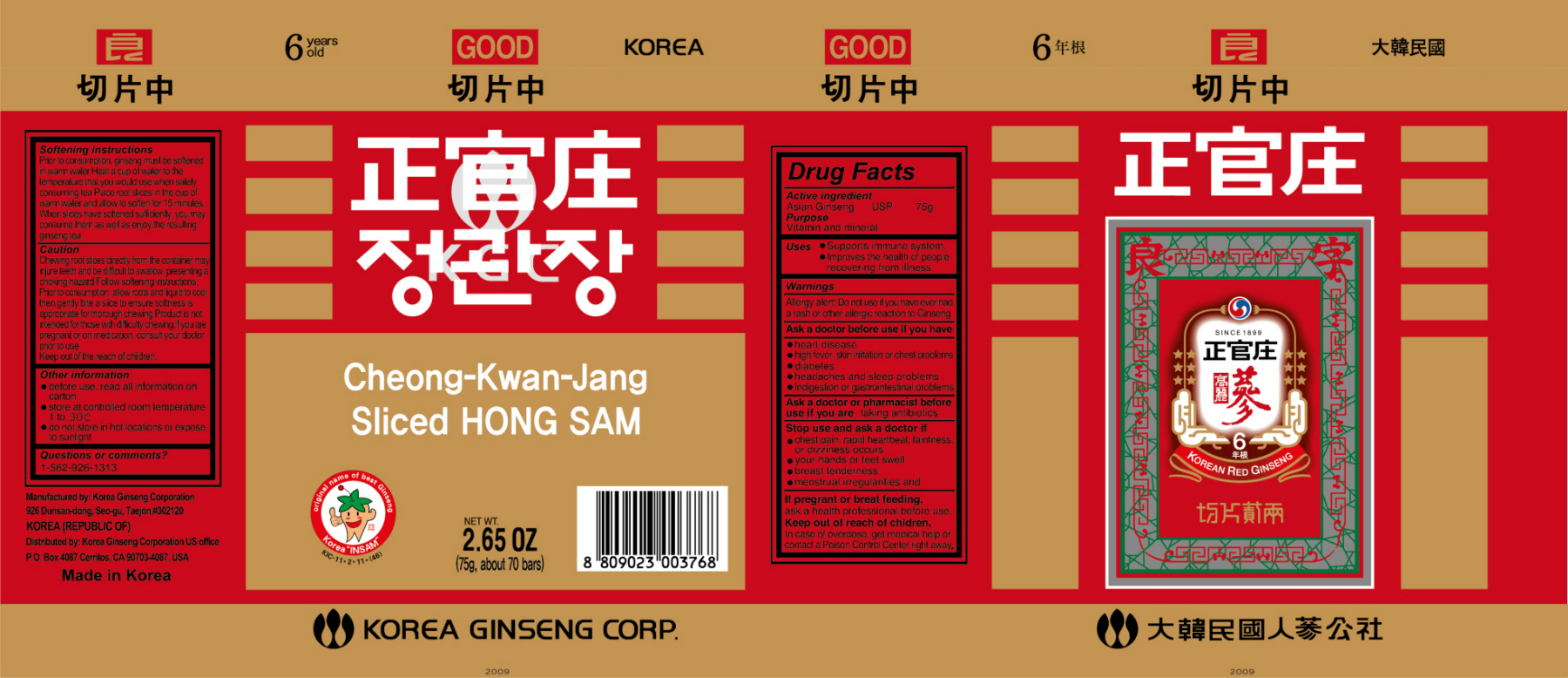 DRUG LABEL: Cheong-Kwan-Jang Sliced Korean HongSam
NDC: 51918-1005 | Form: BAR, CHEWABLE
Manufacturer: Korea Ginseng Corporation
Category: otc | Type: HUMAN OTC DRUG LABEL
Date: 20110531

ACTIVE INGREDIENTS: ASIAN GINSENG 75 g/75 g

Cheong-Kwan-Jang Sliced Korean HongSam

Drug Facts

Active Ingredient
Asian Ginseng USP 75g

Purpose

vitamin and mineral

Keep out of Reach of Children

Stop use and ask a doctor if
- chest pain, rapid heartbeat, faintness or dizziness occurs
- your hands or feet swell
- breast tenderness
- menstrual irregularities
- If pregnant or breast feeding, ask a health professional before use.
- Keep out of reach of children. In case of overdose, get medical help or contact a Poison Control Center right away.

Indication & Usage

Uses
- Supports immune system
- Improves the health of people recovering from illness.
Other information
- before use, read all information on carton
- store at controlled room temperature 1 to 30 ℃
- do not store in hot location or expose to sunlight.

Warnings

Allergy alert: Do not use if you have ever had a rash or other allergic reaction to Ginseng
Ask a doctor before use if you have
-heart disease
-high fever, skin imitation or chest problems
-diabetes
-headaches and sleep problems
-indigestion or gastrointestinal problems
Ask a doctor or pharmacist before use if you are taking antibiotics.

Dosage & Administraion

Softening Instructions
Prior to consumption, ginseng must be softened in warm water.
Heat a cup of water to the temperature that you would use when safely consuming tea.
Place root slices in the cup of warm water and allow to soften for 15 minutes.
When slices have softened sufficiently, you may consume them as well as enjoy the resulting ginseng tea.
Caution
Chewing root slices directly from the container may injure teeth and be difficult to swallow, presenting a choking hazard.
Follow softening instructions.
Prior to consumption, allow roots and liquid to cool, then gently bite a slice to ensure softness is appropriate for thorough chewing.
Product is not intended for those with difficulty chewing.
If you are pregnant or on medication, consult your doctor prior to use.

Inactive Ingredient

Korean Red Ginseng

Korea Ginseng Corporation

Cheong-Kwan-Jang Sliced Korean HongSam
Net WT. 2.65 OZ (75g, about 70 bars)